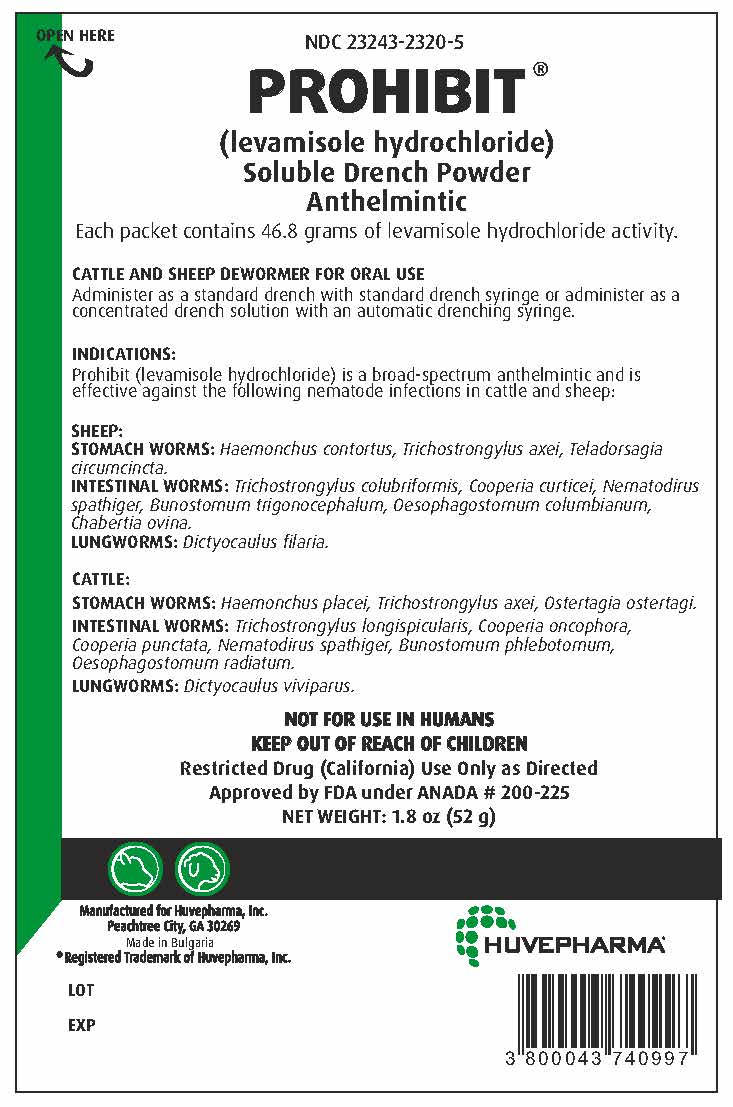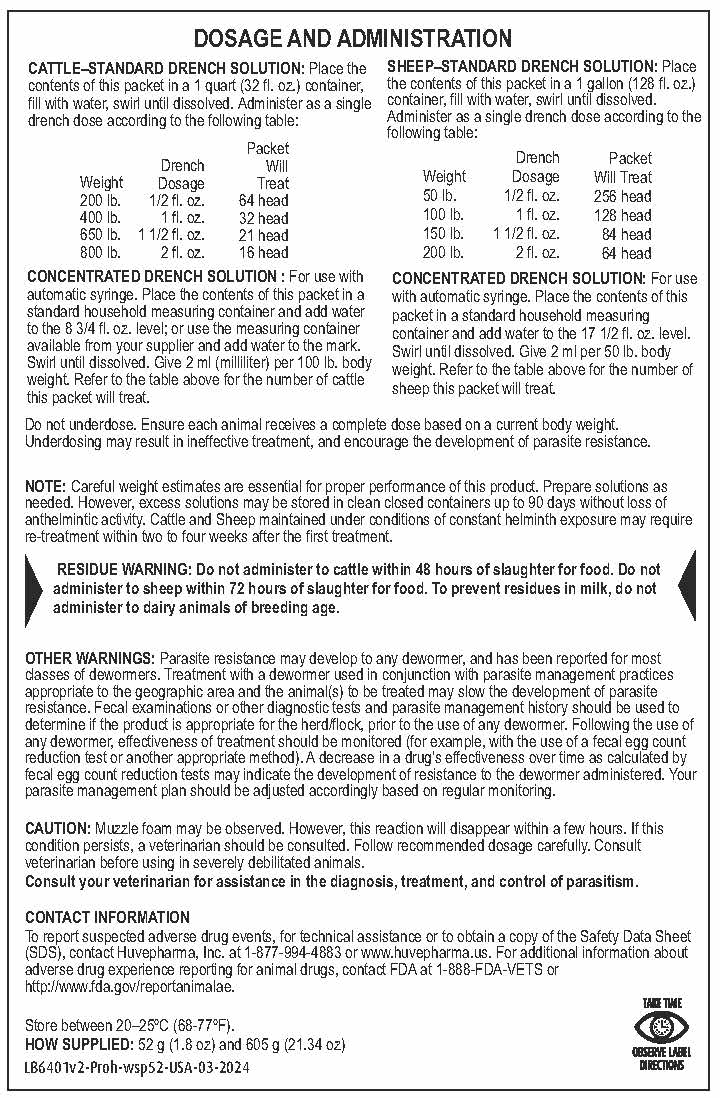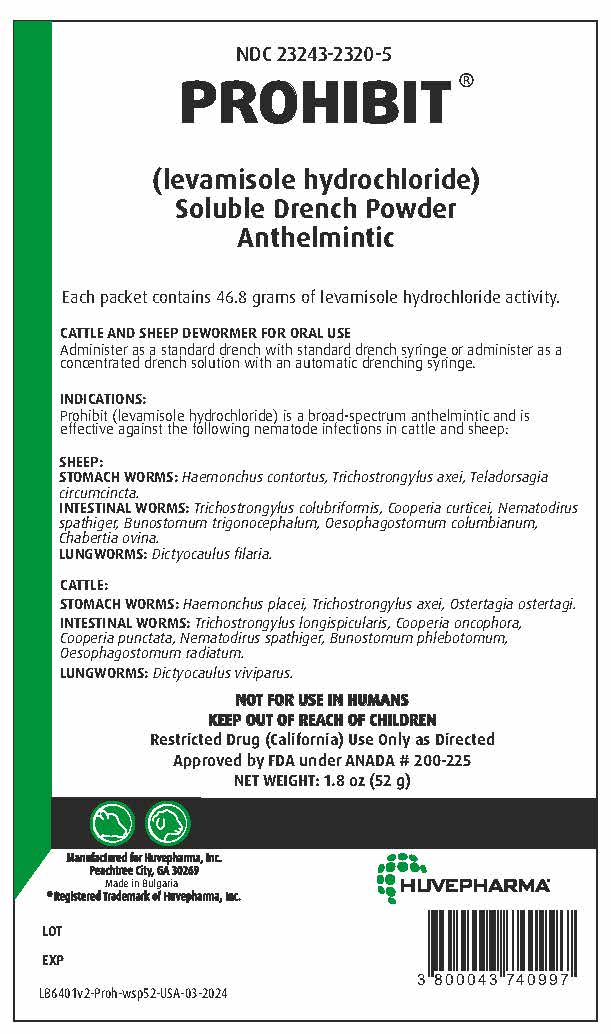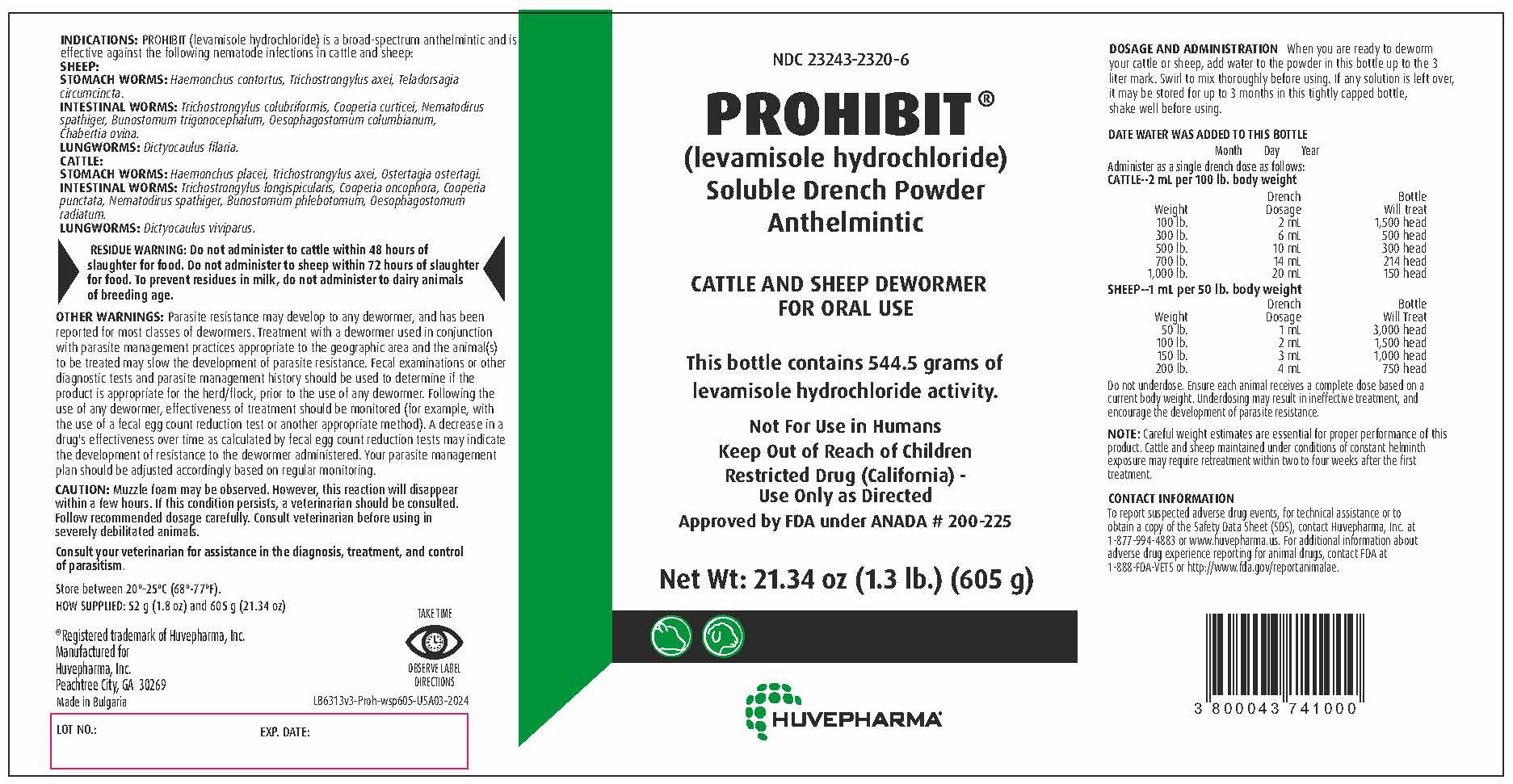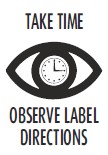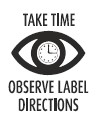 DRUG LABEL: PROHIBIT
NDC: 23243-2320 | Form: POWDER, FOR SOLUTION
Manufacturer: Huvepharma, Inc
Category: animal | Type: OTC ANIMAL DRUG LABEL
Date: 20240528

ACTIVE INGREDIENTS: LEVAMISOLE HYDROCHLORIDE 0.9 g/1 g

NDC 23243-2320-5
PROHIBIT®
(levamisole hydrochloride)
Soluble Drench Powder
Anthelmintic
Each packet contains 46.8 grams of levamisole hydrochloride activity.

VETERINARY INDICATIONS

CATTLE AND SHEEP DEWORMER FOR ORAL USE
Administer as a standard drench with standard drench syringe or administer as a concentrated
drench solution with an automatic drenching syringe.

INDICATIONS:
Prohibit (levamisole hydrochloride) is a broad-spectrum anthelmintic and is effective against
the following nematode infections in cattle and sheep:

SHEEP:
STOMACH WORMS: Haemonchus contortus, Trichostrongylus axei, Teladorsagia circumcincta.
INTESTINAL WORMS: Trichostrongylus colubriformis, Cooperia curticei, Nematodirus spathiger,
Bunostomum trigonocephalum, Oesophagostomum columbianum, Chabertia ovina.
LUNGWORMS: Dictyocaulus filaria.

CATTLE:
STOMACH WORMS: Haemonchus placei, Trichostrongylus axei, Ostertagia ostertagi.
INTESTINAL WORMS: Trichostrongylus longispicularis, Cooperia oncophora, Cooperia punctata,
Nematodirus spathiger, Bunostomum phlebotomum, Oesophagostomum radiatum.
LUNGWORMS: Dictyocaulus viviparus.

GENERAL PRECAUTIONS

NOT FOR USE IN HUMANS
KEEP OUT OF REACH OF CHILDREN
Restricted Drug (California) Use Only as Directed
Approved by FDA under ANADA # 200-225

NET WEIGHT: 1.8 oz (52 g)

HUVEPHARMA®

Manufactured for Huvepharma, Inc.
Peachtree City, GA 30269
Made in Bulgaria
®Registered Trademark of Huvepharma, Inc.

LOT

EXP

DOSAGE AND ADMINISTRATION

CATTLE–STANDARD DRENCH SOLUTION: Place the contents of this packet in a 1 quart (32 fl. oz.) container, fill with water, swirl until dissolved. Administer as a single drench dose according to the following table: |  |  | SHEEP–STANDARD DRENCH SOLUTION: Place the contents of this packet in a 1 gallon (128 fl. oz.) container, fill with water, swirl until dissolved. Administer as a single drench dose according to the following table:
Weight | Drench dosage | Packet Will Treat | Weight | Drench Dosage | Packet Will Treat
200 lb. | 1/2 fl. oz. | 64 head | 50 lb. | 1/2 fl. oz. | 256 head
400 lb. | 1 fl. oz. | 32 head | 100 lb. | 1 fl. oz. | 128 head
650 lb. | 1 1/2 fl. oz. | 21 head | 150 lb. | 1 1/2 fl. oz. | 84 head
800 lb. | 2 fl. oz. | 16 head | 200 lb. | 2 fl. oz. | 64 head

CONCENTRATED DRENCH SOLUTION: For use with automatic syringe. Place the contents of this packet in a standard household measuring container and add water to the 8 3/4 fl. oz. level; or use the measuring container available from your supplier and add water to the mark. Swirl until dissolved. Give 2 ml (milliliter) per 100 lb. body weight. Refer to the table above for the number of cattle this packet will treat. | CONCENTRATED DRENCH SOLUTION: For use with automatic syringe. Place the contents of this packet in a standard household measuring container and add water to the 17 1/2 fl. oz. level. Swirl until dissolved. Give 2 ml per 50 lb. body weight. Refer to the table above for the number of sheep this packet will treat.

Do not underdose. Ensure each animal receives a complete dose based on a current body weight.
Underdosing may result in ineffective treatment, and encourage the development of parasite resistance.

NOTE: Careful weight estimates are essential for proper performance of this product. Prepare solutions
as needed. However, excess solutions may be stored in clean closed containers up to 90 days without
loss of anthelmintic activity. Cattle and Sheep maintained under conditions of constant helminth
exposure may require re-treatment within two to four weeks after the first treatment.

RESIDUE WARNING

RESIDUE WARNING: Do not administer to cattle within 48 hours of slaughter for food. Do
not administer to sheep within 72 hours of slaughter for food. To prevent residues in milk,
do not administer to dairy animals of breeding age.

WARNINGS

OTHER WARNINGS: Parasite resistance may develop to any dewormer, and has been
reported for most classes of dewormers. Treatment with a dewormer used in
conjunction with parasite management practices appropriate to the geographic
area and the animal(s) to be treated may slow the development of parasite
resistance. Fecal examinations or other diagnostic tests and parasite
management history should be used to determine if the product is appropriate
for the herd/flock, prior to the use of any dewormer. Following the use of any
dewormer, effectiveness of treatment should be monitored (for example, with
the use of a fecal egg count reduction test or another appropriate method).
A decrease in a drug's effectiveness over time as calculated by fecal egg
count reduction tests may indicate the development of resistance to the
dewormer administered. Your parasite management plan should be adjusted
accordingly based on regular monitoring.

GENERAL PRECAUTIONS

CAUTION: Muzzle foam may be observed. However, this reaction will
disappear within a few hours. If this condition persists, a veterinarian
should be consulted. Follow recommended dosage carefully. Consult
veterinarian before using in severely debilitated animals.
Consult your veterinarian for assistance in the diagnosis, treatment,
and control of parasitism.

ADVERSE REACTIONS

CONTACT INFORMATION

To report suspected adverse drug events, for technical assistance or to
obtain a copy of the Safety Data Sheet (SDS), contact Huvepharma, Inc.
at 1-877-994-4883 or www.huvepharma.us. For additional information about
adverse drug experience reporting for animal drugs, contact FDA at
1-888-FDA-VETS or http://www.fda.gov/reportanimalae.

STORAGE AND HANDLING

Store between 20–25ºC (68-77ºF).
HOW SUPPLIED: 52 g (1.8 oz) and 605 g (21.34 oz)

NDC 23243-2320-6
PROHIBIT®
(levamisole hydrochloride)
Soluble Drench Powder
Anthelmintic

VETERINARY INDICATIONS

CATTLE AND SHEEP DEWORMER FOR ORAL USE
This bottle contains 544.5 grams of levamisole hydrochloride activity.

GENERAL PRECAUTIONS

Not For Use in Humans

Keep Out of Reach of Children

Restricted Drug (California) - Use Only as Directed

Approved by FDA under ANADA # 200-225

Net Wt: 21.34 oz (1.3 lb.) (605 g)

VETERINARY INDICATIONS

INDICATIONS: PROHIBIT (levamisole hydrochloride) is a broad-spectrum anthelmintic and is
effective against the following nematode infections in cattle and sheep:
SHEEP:
STOMACH WORMS: Haemonchus contortus, Trichostrongylus axei, Teladorsagia circumcincta.
INTESTINAL WORMS: Trichostrongylus colubriformis, Cooperia curticei, Nematodirus spathiger,
Bunostomum trigonocephalum, Oesophagostomum columbianum, Chabertia ovina.
LUNGWORMS: Dictyocaulus filaria.
CATTLE:
STOMACH WORMS: Haemonchus placei, Trichostrongylus axei, Ostertagia ostertagi.
INTESTINAL WORMS: Trichostrongylus longispicularis, Cooperia oncophora, Cooperia punctata,
Nematodirus spathiger, Bunostomum phlebotomum, Oesophagostomum radiatum.
LUNGWORMS: Dictyocaulus viviparus.

RESIDUE WARNING

RESIDUE WARNING: Do not administer to cattle within 48 hours of slaughter
for food. Do not administer to sheep within 72 hours of slaughter for food. To
prevent residues in milk, do not administer to dairy animals of breeding age.

WARNINGS

OTHER WARNINGS: Parasite resistance may develop to any dewormer, and has been reported
for most classes of dewormers. Treatment with a dewormer used in conjunction with parasite
management practices appropriate to the geographic area and the animal(s) to be treated may
slow the development of parasite resistance. Fecal examinations or other diagnostic tests and
parasite management history should be used to determine if the product is appropriate for the
herd/flock, prior to the use of any dewormer. Following the use of any dewormer, effectiveness
of treatment should be monitored (for example, with the use of a fecal egg count reduction
test or another appropriate method). A decrease in a drug's effectiveness over time as
calculated by fecal egg count reduction tests may indicate the development of resistance to
the dewormer administered. Your parasite management plan should be adjusted accordingly
based on regular monitoring.

GENERAL PRECAUTIONS

CAUTION: Muzzle foam may be observed. However, this reaction will disappear within a few
hours. If this condition persists, a veterinarian should be consulted. Follow recommended
dosage carefully. Consult veterinarian before using in severely debilitated animals.

Consult your veterinarian for assistance in the diagnosis, treatment, and control of parasitism.

STORAGE AND HANDLING

Store between 20º-25ºC (68º-77ºF).

HOW SUPPLIED: 52 g (1.8 oz) and 605 g (21.34 oz)

®Registered trademark of Huvepharma, Inc.
Manufactured for
Huvepharma, Inc.
Peachtree City, GA 30269
Made in Bulgaria

LOT NO.: EXP. DATE

DOSAGE AND ADMINISTRATION: When you are ready to deworm your cattle or sheep, add water to the powder in this bottle up to the 3 liter mark. Swirl to mix thoroughly before using. If any solution is left over, it may be stored for up to 3 months in this tightly capped bottle, shake well before using.

DATE WATER WAS ADDED TO THIS BOTTLE

Month Day Year

Administer as a single drench dose as follows:
CATTLE--2 mL per 100 lb. body weight
Weight | Drench dosage | Bottle; Will Treat
100 lb. | 2 mL | 1,500 head
300 lb. | 6 mL | 500 head
500 lb. | 10 mL | 300 head
700 lb. | 14 mL | 214 head
1,000 lb. | 20 mL | 150 head
SHEEP--1 mL per 50 lb. body weight
Weight | Drench dosage | Bottle; Will Treat
50 lb. | 1 mL | 3,000 head
100 lb. | 2 mL | 1,500 head
150 lb. | 3 mL | 1,000 head
200 lb. | 4 mL | 750 head

Do not underdose. Ensure each animal receives a complete dose based on a current body weight.
Underdosing may result in ineffective treatment, and encourage the development of parasite resistance.

NOTE: Careful weight estimates are essential for proper performance of this
product. Cattle and sheep maintained under conditions of constant helminth
exposure may require retreatment within two to four weeks after the first
treatment.

ADVERSE REACTIONS

CONTACT INFORMATION

To report suspected adverse drug events, for technical assistance or to
obtain a copy of the Safety Data Sheet (SDS), contact Huvepharma, Inc. at
1-877-994-4883 or www.huvepharma.us. For additional information about
adverse drug experience reporting for animal drugs, contact FDA at
1-888-FDA-VETS or http://www.fda.gov/reportanimalae.